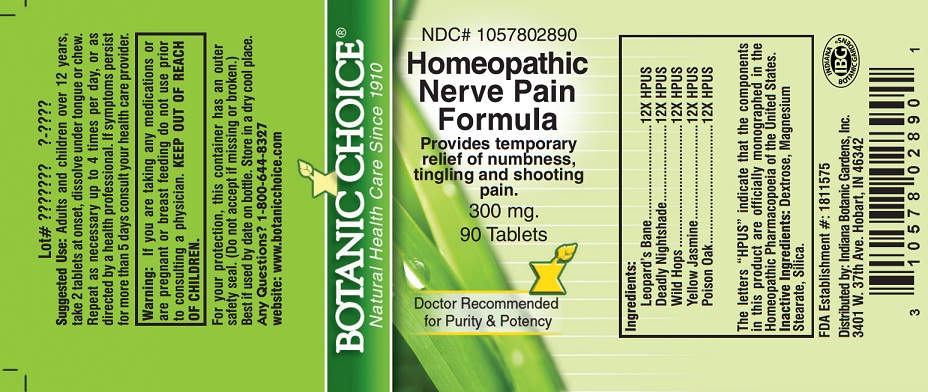 DRUG LABEL: Homeopathic Nerve Pain
NDC: 10578-028 | Form: TABLET
Manufacturer: Indiana Botanic Gardens
Category: homeopathic | Type: HUMAN OTC DRUG LABEL
Date: 20130401

ACTIVE INGREDIENTS: ARNICA MONTANA 12 [hp_X]/1 1; ATROPA BELLADONNA 12 [hp_X]/1 1; BRYONIA ALBA ROOT 12 [hp_X]/1 1; GELSEMIUM SEMPERVIRENS ROOT 12 [hp_X]/1 1; TOXICODENDRON PUBESCENS LEAF 12 [hp_X]/1 1
INACTIVE INGREDIENTS: DEXTROSE; MAGNESIUM STEARATE; SILICON DIOXIDE

Homeopathic Nerve Pain

Suggested Use:

Adults and children over 12 years, take 2 tablets at onset, dissolve under tongue or chew. Repeat as necessary up to 4 times per day, or as directed by a health professional.

STOP USE

If symptoms persist for more than 5 days consult your health care provider.

Warning:

If you are taking any medications or are pregnant or breast feeding do not use prior to consulting a physician.

KEEP OUT OF REACH OF CHILDREN.

For your protection, this container has an outer safety seal. (Do not accept if missing or broken.) Best if used by date on bottle. Store in a dry cool place.

Any Questions?

Any Questions? 1-800-644-8327

website: www.botanicchoice.com

PURPOSE

INDICATIONS AND USAGE

Provides temporary relief of numbness, tingling and shooting pain.

Ingredients:

Leopard’s Bane ...........................12X HPUS

Deadly Nightshade ......................12X HPUS

Wild Hops ...................................12X HPUS

Yellow Jasmine ...........................12X HPUS

Poison Oak ..................................12X HPUS

The letters “HPUS” indicate that the components in this product are officially monographed in the Homeopathic Pharmacopoeia of the United States.

Inactive Ingredients:

Dextrose, Magnesium Stearate, Silica.

FDA Establishment #: 1811575

Distributed by: Indiana Botanic Gardens, Inc.

3401 W. 37th Ave. Hobart, IN 46342

Botanic Choice®

Natural Health Care Since 1910

NDC# 1057802890

Homeopathic Nerve Pain Formula

Provides temporary relief of numbness, tingling and shooting pain.

300 mg.

90 Tablets

Doctor Recommended for Purity & Potency